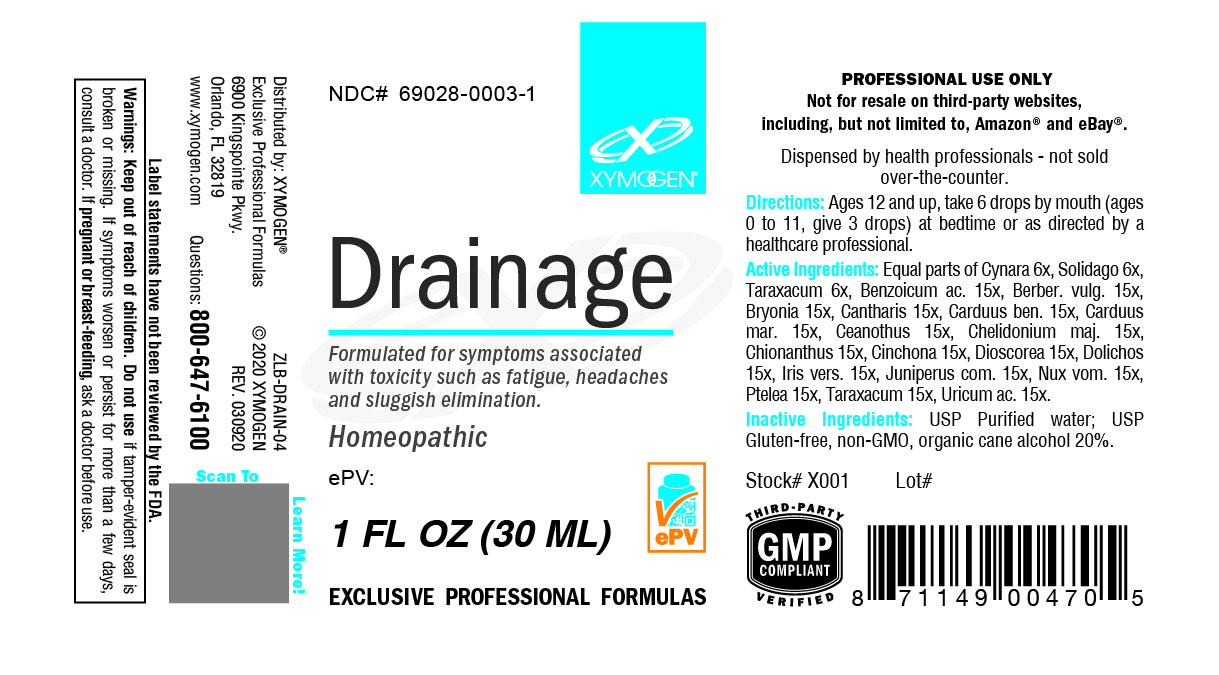 DRUG LABEL: Drainage
NDC: 69028-0003 | Form: LIQUID
Manufacturer: Xymogen
Category: homeopathic | Type: HUMAN OTC DRUG LABEL
Date: 20200508

ACTIVE INGREDIENTS: CYNARA SCOLYMUS LEAF 6 [hp_X]/1 mL; BENZOIC ACID 15 [hp_X]/1 mL; BERBERIS VULGARIS ROOT BARK 15 [hp_X]/1 mL; BRYONIA ALBA ROOT 15 [hp_X]/1 mL; LYTTA VESICATORIA 15 [hp_X]/1 mL; CENTAUREA BENEDICTA 15 [hp_X]/1 mL; MILK THISTLE 15 [hp_X]/1 mL; CEANOTHUS AMERICANUS LEAF 15 [hp_X]/1 mL; CHELIDONIUM MAJUS 15 [hp_X]/1 mL; CINCHONA OFFICINALIS BARK 15 [hp_X]/1 mL; DIOSCOREA VILLOSA TUBER 15 [hp_X]/1 mL; CHIONANTHUS VIRGINICUS BARK 15 [hp_X]/1 mL; MUCUNA PRURIENS FRUIT TRICHOME 15 [hp_X]/1 mL; IRIS VERSICOLOR ROOT 15 [hp_X]/1 mL; JUNIPER BERRY 15 [hp_X]/1 mL; STRYCHNOS NUX-VOMICA SEED 15 [hp_X]/1 mL; PTELEA TRIFOLIATA BARK 15 [hp_X]/1 mL; TARAXACUM OFFICINALE 15 [hp_X]/1 mL; URIC ACID 15 [hp_X]/1 mL; SOLIDAGO VIRGAUREA FLOWERING TOP 6 [hp_X]/1 mL
INACTIVE INGREDIENTS: WATER; ALCOHOL

Drainage 0003L

INDICATIONS & USAGE SECTION

Formulated for symptoms associated with toxicity such as fatigue, headaches and sluggish elimination..

DOSAGE & ADMINISTRATION SECTION

Directions: Ages 12 and up, take 6 drops by mouth (ages 0 to 11, give 3 drops) at bedtime or as directed by a healthcare professional.

OTC - ACTIVE INGREDIENT SECTION

Equal parts of Cynara 6x, Solidago 6x, Taraxacum 6x, Benzoicum ac. 15x, Berber. vulg. 15x, Bryonia 15x, Cantharis 15x, Carduus ben. 15x, Carduus mar. 15x, Ceanothus 15x, Chelidonium maj. 15x, Chionanthus 15x, Cinchona 15x, Dioscorea 15x, Dolichos 15x, Iris vers. 15x, Juniperus com. 15x, Nux. vom. 15x, Ptelea 15x, Taraxacum 15x, Uricum ac. 15x.

OTC - PURPOSE SECTION

Formulated for symptoms associated with toxicity such as fatigue, headaches and sluggish elimination.

INACTIVE INGREDIENT SECTION

Inactive Ingredients: USP Purified Water; USP Gluten-free, non-GMO, organic cane alcohol 20%.

QUESTIONS SECTION

www.xymogen.com - Questions? 800-647-6100

Xymogen

6900 Kingspointe Pkwy.

Orlando, FL 32819

WARNINGS SECTION

WARNINGS: Keep out of reach of children. Do not use if tamper-evident seal is broken or missing. If symptoms worsen or persist for more than a few days, consult a doctor. If pregnant or breast-feeding, ask a doctor before use.

OTC - PREGNANCY OR BREAST FEEDING SECTION

If pregnant or breast-feeding, ask a doctor before use.

OTC - KEEP OUT OF REACH OF CHILDREN SECTION

Keep out of reach of children.